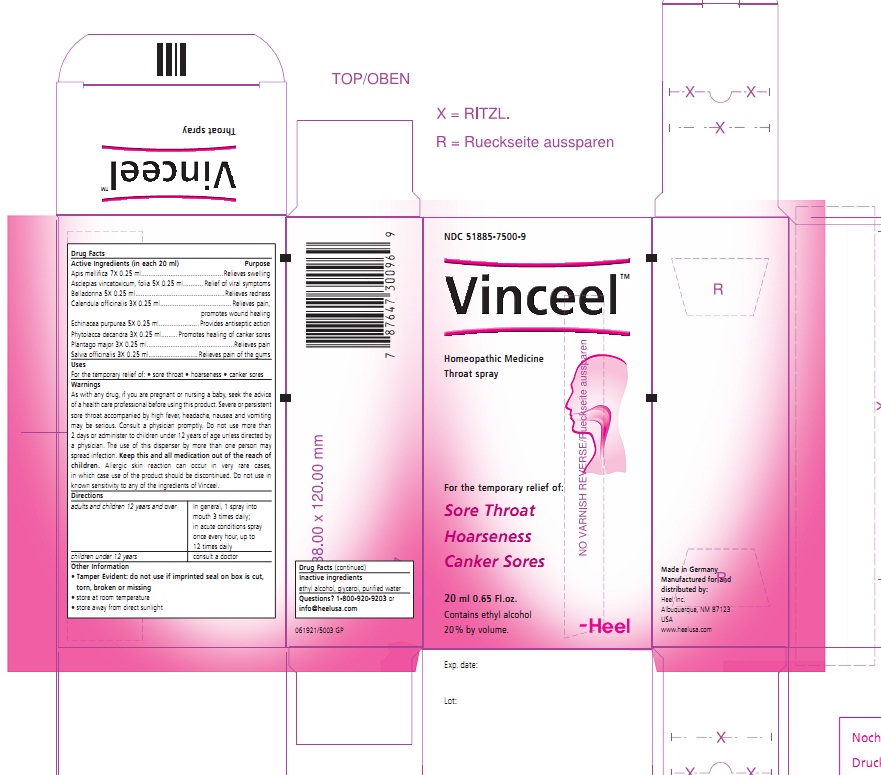 DRUG LABEL: Vinceel 
NDC: 51885-7500 | Form: SPRAY
Manufacturer: Biologische Heilmittel Heel
Category: homeopathic | Type: HUMAN OTC DRUG LABEL
Date: 20120305

ACTIVE INGREDIENTS: APIS MELLIFERA 7 [hp_X]/20 mL; CYNANCHUM VINCETOXICUM LEAF 5 [hp_X]/20 mL; ATROPA BELLADONNA 5 [hp_X]/20 mL; CALENDULA OFFICINALIS FLOWERING TOP 3 [hp_X]/20 mL; ECHINACEA PURPUREA 5 [hp_X]/20 mL; PHYTOLACCA AMERICANA ROOT 3 [hp_X]/20 mL; PLANTAGO MAJOR 3 [hp_X]/20 mL; SAGE 3 [hp_X]/20 mL
INACTIVE INGREDIENTS: ALCOHOL; GLYCERIN; WATER

VINCEEL THROAT SPRAY

PURPOSE

Apis mellifica 7X 0.25 ml....................................Relieves swelling
Asclepias vincetoxicum , folia 5X 0.25 ml............Relief of viral symptoms
Belladonna 5X 0.25 ml........................................Relieves redness
Calendula officinalis 3X 0.25 ml...........................Relieves pain, promotes wound healing
Echinacea purpurea 5X 0.25 ml...........................Provides antiseptic action
Phytolacca decandra 3X 0.25 ml.........................Promotes healing of canker sores
Plantago major 3X 0.25 ml..................................Relieves pain
Salvia officinalis 3X 0.25 ml................................Relieves pain of the gums

KEEP OUT OF REACH OF CHILDREN

Keep this and all medicines out of the reach of children

INDICATIONS AND USAGE

For the temporary relief of:

- Sore throat
- Hoarseness
- Canker sores

WARNINGS

As with any drug, if you are pregnant or nursing a baby, seek the advise of a health care professional before using this product. Severe or persistent sore throat accompanied by high fever, headache, nausea and vomiting may be serious. Consult a physician promptly. Do not use more than 2 days or administer to children under 12 years of age unless directed by a physician. The use of this dispenser by more than one person may spread infection. Keep this and all medication out of the reach of children. Allergic skin reaction can occur in vary rare cases, in which case use of the product should be discontinued. Do not use in known sensitivity to any of the ingredients of Vinceel.

DOSAGE AND ADMINISTRATION

Adults and children 12 years and over: In general, 1 spray into mouth 3 times daily; in acute conditions spray once every hour, up to 12 times daily

Children under 12 years: Consult a doctor

ACTIVE INGREDIENTS

Each 20 ml contains as active ingredients: Apis mellifica 7X 0.25 ml, Asclepias vincetoxicum , folia 5X 0.25 ml, Belladonna 5X 0.25 ml, Calendula officinalis 3X 0.25 ml, Echinacea purpurea 5X 0.25 ml, Phytolacca decandra 3X 0.25 ml, Plantago major 3X 0.25 ml, Salvia officinalis 3X 0.25 ml

INACTIVE INGREDIENTS

Ethyl alcohol, glycerol, purified water